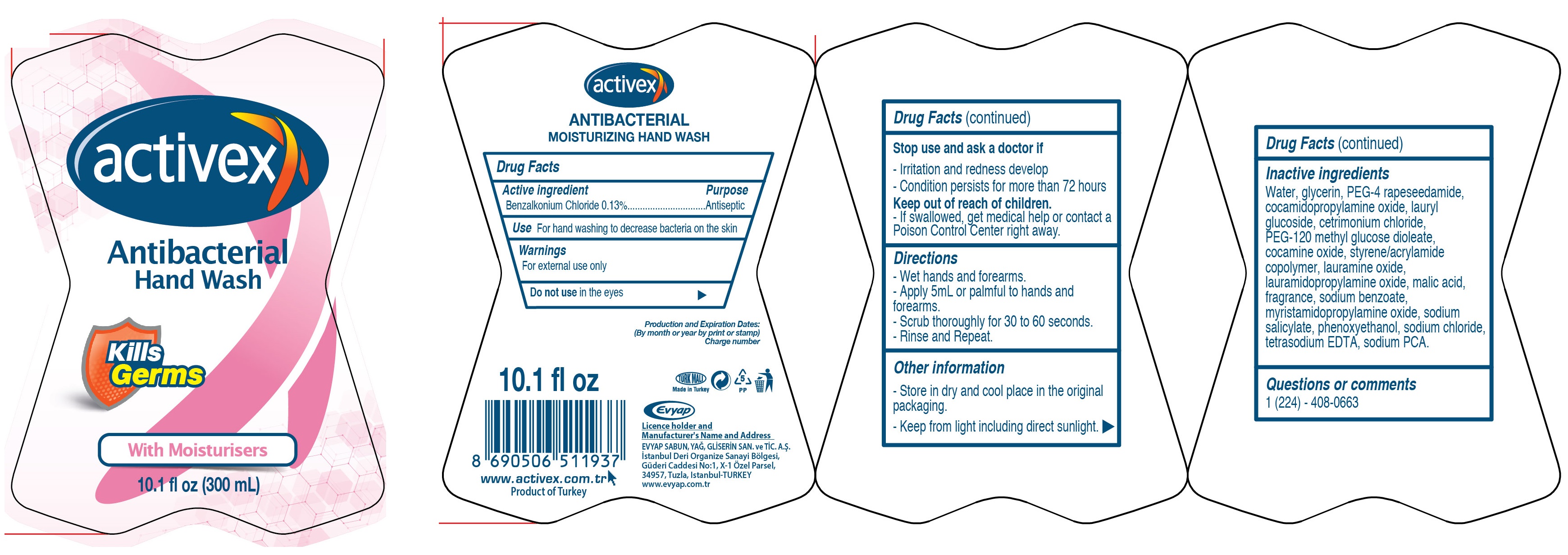 DRUG LABEL: Activex Antibacterial Hand Wash
NDC: 64309-002 | Form: LIQUID
Manufacturer: Evyap Sabun Yag Gliserin Sanayi Ve Ticaret Anonim Sirketi
Category: otc | Type: HUMAN OTC DRUG LABEL
Date: 20201026

ACTIVE INGREDIENTS: BENZALKONIUM CHLORIDE 1.3 mg/1 mL
INACTIVE INGREDIENTS: WATER; GLYCERIN; PEG-4 RAPESEEDAMIDE; COCAMIDOPROPYLAMINE OXIDE; LAURYL GLUCOSIDE; CETRIMONIUM CHLORIDE; PEG-120 METHYL GLUCOSE DIOLEATE; COCAMINE OXIDE; STYRENE/ACRYLAMIDE COPOLYMER (500000 MW); LAURAMINE OXIDE; LAURAMIDOPROPYLAMINE OXIDE; MALIC ACID; SODIUM BENZOATE; MYRISTAMIDOPROPYLAMINE OXIDE; SODIUM SALICYLATE; PHENOXYETHANOL; SODIUM CHLORIDE; EDETATE SODIUM; SODIUM PYRROLIDONE CARBOXYLATE

Activex Antibacterial Hand Wash

Active ingredient

Benzalkonium Chloride 0.13%

Purpose

Antiseptic

Use

For hand washing to decrease bacteria on the skin

Warnings

For external use only

Do not use

in the eyes

Stop use and ask a doctor if

- Irritation and redness develop

- Condition persists for more than 72 hours

Keep out of reach of children.

- If swallowed, get medical help or contact a Poison Control Center right away.

Directions

- Wet hands and forearms.

- Apply 5mL or palmful to hands and forearms.

- Scrub thoroughly for 30 to 60 seconds.

- Rinse and Repeat.

Other information

- Store in dry and cool place in the original packaging.

- Keep from light including direct sunlight.

Inactive ingredients

Water, glycerin, PEG-4 rapeseedamide, cocamidopropylamine oxide, lauryl glucoside, cetrimonium chloride, PEG-120 methyl glucose dioleate, cocamine oxide, styrene/acrylamide copolymer, lauramine oxide, lauramidopropylamine oxide, malic acid, fragrance, sodium benzoate, myristamidopropylamine oxide, sodium salicylate, phenoxyethanol, sodium chloride, tetrasodium EDTA, sodium PCA.

Questions or comments

1 (224) - 408-0663